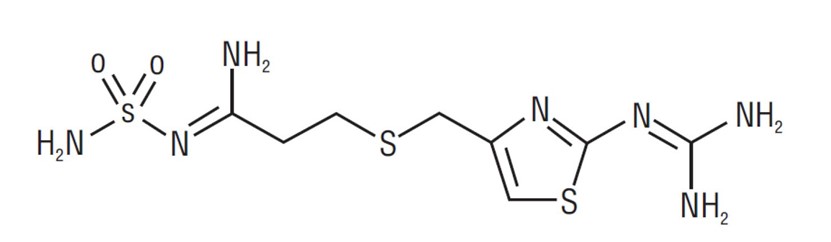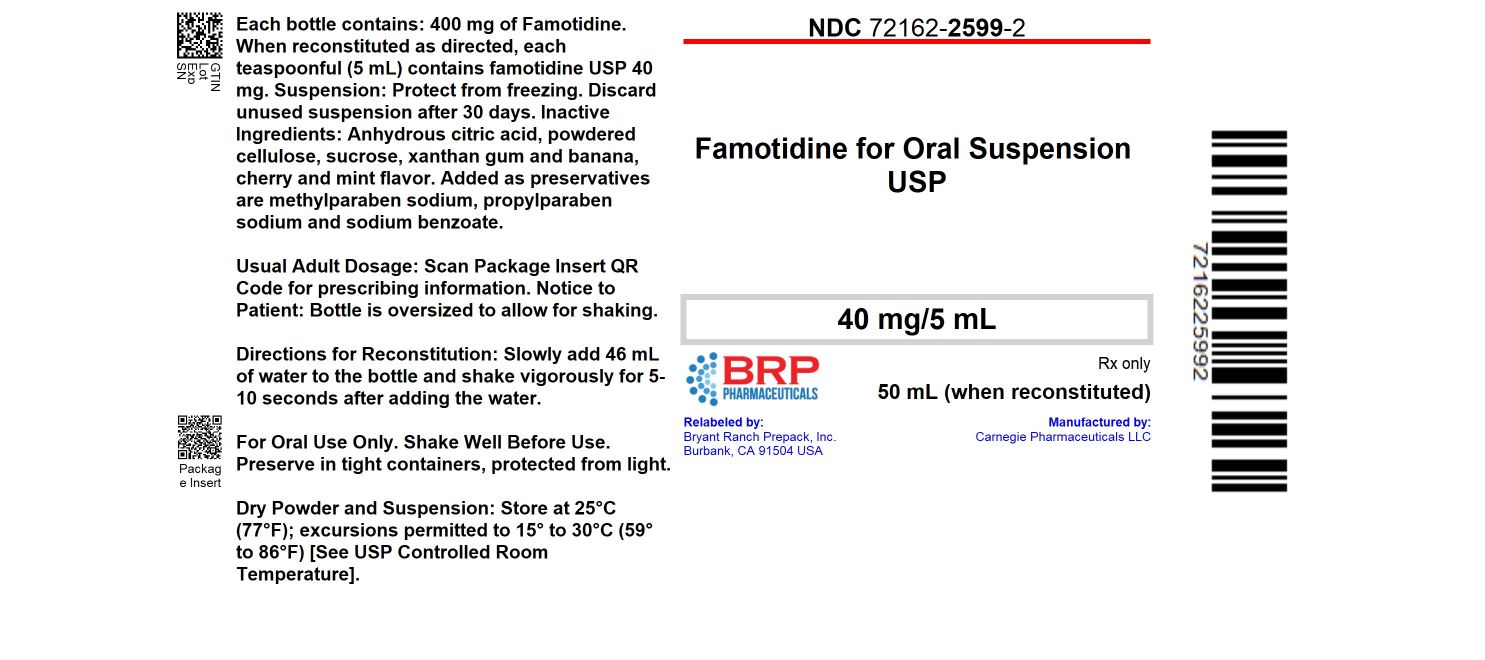 DRUG LABEL: FAMOTIDINE
NDC: 72162-2599 | Form: POWDER, FOR SUSPENSION
Manufacturer: Bryant Ranch Prepack
Category: prescription | Type: HUMAN PRESCRIPTION DRUG LABEL
Date: 20260109

ACTIVE INGREDIENTS: FAMOTIDINE 40 mg/5 mL
INACTIVE INGREDIENTS: ANHYDROUS CITRIC ACID; POWDERED CELLULOSE; SUCROSE; XANTHAN GUM; METHYLPARABEN SODIUM; PROPYLPARABEN SODIUM; SODIUM BENZOATE

HIGHLIGHTS OF PRESCRIBING INFORMATION

These highlights do not include all the information needed to use FAMOTIDINE FOR ORAL SUSPENSION safely and effectively.
See full prescribing information for FAMOTIDINE FOR ORAL SUSPENSION.
FAMOTIDINE for oral suspension
Initial U.S. Approval: 1986

1 INDICATIONS AND USAGE

Famotidine for oral suspension is a histamine-2 (H2) receptor antagonist indicated (1):

In adults for the treatment of:

- active duodenal ulcer (DU).
- active gastric ulcer (GU).
- symptomatic nonerosive gastroesophageal reflux disease (GERD).
- erosive esophagitis due to GERD, diagnosed by biopsy.
- treatment of pathological hypersecretory conditions (e.g., Zollinger-Ellison syndrome, multiple endocrine neoplasias).
- reduction of the risk of DU recurrence.

In pediatric patients 1 year of age and older for the treatment of:

- peptic ulcer
- GERD with or without esophagitis and ulcerations

In pediatric patients from birth to less than 1 year of age for the treatment of:

- GERD.

2 DOSAGE AND ADMINISTRATION

- Recommended adult dosage by indication (2.1):

Active DU | 40 mg once daily; or; 20 mg twice daily
Active GU | 40 mg once daily
Symptomatic Nonerosive GERD | 20 mg twice daily
Erosive Esophagitis due to GERD | 20 mg twice daily; or; 40 mg twice daily
Pathological Hypersecretory; Conditions | 20 mg every 6 hours; adjust to patient needs; maximum 160 mg every 6 hours
Risk Reduction of DU Recurrence | 20 mg once daily

- Recommended pediatric dosage by indication (2.2):

Peptic Ulcer Disease | 1 year to less than 17 years; Starting dosage 0.5 mg/kg once daily; or; 0.25 mg/kg twice daily; may increase to 1 mg/kg; once daily at bedtime or 0.5 mg/kg twice daily; Maximum of 40 mg per day
GERD | Birth to less than 3 months; Starting dosage 0.5 mg/kg once daily; may; increase to 1 mg/kg once daily
GERD | 3 months to less than 1 year; Starting dosage 0.5 mg/kg twice daily; may; increase to 1 mg/kg twice daily; Maximum of; 40 mg per day
GERD with or; without esophagitis; and ulcerations | 1 year to less than 17 years; 0.5 mg/kg twice daily Maximum of 40 mg twice daily

- See full prescribing information for complete dosing information in adults and pediatrics, recommended treatment duration by indication, and dosage adjustment for adult patients with renal impairment. (2.1, 2.2, 2.3)

Administration (2.3):

- Take once daily before bedtime or twice daily in the morning and before bedtime with or without food.

3 DOSAGE FORMS AND STRENGTHS

For oral suspension: 40 mg/5 mL (3)

4 CONTRAINDICATIONS

History of serious hypersensitivity reactions (e.g., anaphylaxis) to famotidine or other H2 receptor antagonists. (4)

5 WARNINGS AND PRECAUTIONS

- Central Nervous System (CNS) Adverse Reactions: Elderly patients and patients with renal impairment at increased risk; reduce the dosage. (2.2, 5.1, 8.5, 8.6)
- GI Malignancy: Absence of GI symptoms does not preclude the presence of gastric malignancy; evaluate prior to initiating therapy. (5.2)

6 ADVERSE REACTIONS

The most common adverse reactions are: headache, dizziness, constipation, and diarrhea. (6.1)

To report SUSPECTED ADVERSE REACTIONS, contact Carnegie Pharmaceuticals LLC at 1-732-783-7010 or FDA at 1-800-FDA-1088 or www.fda.gov/medwatch.

7 DRUG INTERACTIONS

- Drugs Dependent on Gastric pH for Absorption: Systemic exposure of the concomitant drug may be significantly reduced leading to loss of efficacy. See full prescribing information for a list of interacting drugs. (7.1)
- Tizanidine (CYP1A2) Substrate: Potential for substantial increases in blood concentrations of tizanidine resulting in hypotension, bradycardia or excessive drowsiness; avoid concomitant use, if possible. (7.2)

8 USE IN SPECIFIC POPULATIONS

- Geriatric Use: Use the lowest effective dose for an elderly patient and monitor renal function. (2.2, 5.1, 8.5)
- Renal Impairment: Risk of CNS adverse reactions and QT prolongation in patients with moderate and severe renal impairment; reduce the dosage in adults. (2.2, 8.6)

FULL PRESCRIBING INFORMATION

1 INDICATIONS AND USAGE

Famotidine for oral suspension is indicated in adults for the treatment of:

- active duodenal ulcer (DU).
- active gastric ulcer (GU).
- symptomatic nonerosive gastroesophageal reflux disease (GERD).
- erosive esophagitis due to GERD, diagnosed by biopsy.
- treatment of pathological hypersecretory conditions (e.g., Zollinger-Ellison syndrome, multiple endocrine neoplasias).
- reduction of the risk of duodenal ulcer recurrence.

Famotidine for oral suspension is indicated in pediatric patients 1 year of age and older for the treatment of:

- peptic ulcer disease.
- GERD with or without esophagitis and ulcerations.

Famotidine for oral suspension is indicated in pediatric patients from birth to less than 1 year of age for the treatment of:

- GERD.

2 DOSAGE AND ADMINISTRATION

2.1 Recommended Dosage in Adults

The recommended dosage and duration of Famotidine for oral suspension in adults with normal renal function is shown in Table 1.

Table 1: Recommended Dosage and Duration of Famotidine for Oral Suspensiona in Adults with Normal Renal Function
Indication | Recommended Dosage | Recommended Duration
Active DU | 40 mg once daily; or 20 mg twice dailyb | Up to 8 weeksc,d
Active GU | 40 mg once daily | Up to 8 weeksd
Symptomatic nonerosive GERD | 20 mg twice daily | Up to 6 weeksd
Erosive esophagitis due to GERD, diagnosed by endoscopy | 20 mg twice daily; or 40 mg twice dailyb | Up to 12 weeks
Pathological hypersecretory conditions | Starting dosage: 20 mg every 6 hours; adjust dosage to individual patient needs; Maximum dosage 160 mg every 6 hours | As clinically indicated
Reduction of the risk of DU recurrence | 20 mg once daily | 1 yearc,d or as clinically indicated

a After preparation, the concentration of famotidine oral suspension is 8 mg/mL [see DOSAGE AND ADMINISTRATION (2.3)]

b Both dosages demonstrated effectiveness in clinical trials [see CLINICAL STUDIES (14)].

c In clinical trials, the majority of patients healed within 4 weeks. For patients who do not heal after 4 weeks, consider an additional 2 to 4 weeks of treatment [see CLINICAL STUDIES (14.1)].

d Longer treatment durations have not been studied in clinical trials [see CLINICAL STUDIES (14.1, 14.2, 14.3)].

2.2 Recommended Dosage in Pediatric Patients

The recommended dosage and duration of famotidine for oral suspension in pediatric patients with normal renal function is shown in Table 2.

Table 2: Recommended Dosage and Duration of Famotidine for Oral Suspensiona in Pediatric Patients with Normal Renal Function
Indication | Pediatric Age Range | Recommended Dosagea | Duration
Peptic Ulcer Disease | 1 year to less than 17 years | Starting dosage 0.5 mg/kg once daily; or 0.25 mg/kg twice daily.; May increase to 1 mg/kg once daily at bedtime or 0.5 mg/ kg twice daily; Maximum of 40 mg per day | 8 weeksb
GERD | Birth to less than 3 months | Starting dosage 0.5 mg/kg once daily. May increase to 1 mg/kg once dailyb | Up to 8 weeksb,c,d
GERD | 3 months to less than 1 year | Starting dosage 0.5 mg/kg twice daily. May increase to 1 mg/kg twice dailyc; Maximum of 40 mg per day | Up to 8 weeksb,c,d
GERD with or without esophagitis and ulcerations | 1 year to less than 17 years | 0.5 mg/kg twice daily; Maximum of 40 mg twice daily | 6 to 12 weeksb

a After preparation, the concentration of famotidine oral suspension is 8 mg/mL [see DOSAGE AND ADMINISTRATION (2.3)]

b Treatment duration based on adult recommendations (see Table 1). Individualize the dose and duration based upon clinical response an/or pH determinations (gastric or esophageal) and endoscopy.

c Use conservative measures (e.g., thickened feedings) concurrently [see USE IN SPECIFIC POPULATIONS (8.4)].

d After 4 weeks of treatment re-evaluate the patient. Consider an additional 4 weeks of treatment if treatment benefit outweighs potential risks.

2.3 Recommended Dosage in Adults with Renal Impairment

Recommended dosage adjustments for adults with moderate to severe renal impairment (creatinine clearance less than 60 mL/min) by indication are shown in Table 3. Use the lowest effective dosage [see USE IN SPECIFIC POPULATIONS (8.6)].

A safe and effective dosage has not been established in pediatric patients with renal impairment.

Table 3: Recommended Maximum Dosage of Famotidine for Oral Suspension in Adults with Moderate and Severe Renal Impairment
Indication | Recommended Maximum Dosages
Indication | Creatinine clearance 30 to 60 mL/minute | Creatinine clearance less than 30 mL/minute
Active DU | 20 mg once daily; or 40 mg every other day | 10 mg once daily; or 20 mg every other day
Active GU | 20 mg once daily; or 40 mg every other day | 10 mg once daily; or 20 mg every other day
Symptomatic nonerosive GERD | 20 mg once daily | 10 mg once daily; or 20 mg every other day
Erosive esophagitis due to GERD, diagnosed by endoscopya | 20 mg once daily; or 40 mg every other dayb; 40 mg once dailyb | 10 mg once daily; or 20 mg every other dayb; 20 mg once dailyb
Pathological hypersecretory conditions | Avoid useb
Reduction of the risk of DU recurrence | 10 mg once daily; or 20 mg every other day | 10 mg every other day

a Dosage adjustments for renal impairment are provided for both dosing regimens (20 mg twice daily and 40 mg twice daily) which showed effectiveness for the treatment of erosive esophagitis in clinical trials [see CLINICAL STUDIES (14.4)].
b The dosage required to treat pathological hypersecretory conditions may exceed the maximum dosage evaluated in patients with impaired renal function. The risk for increased adverse reactions in renally impaired patients treated with famotidine for oral suspension for pathological hypersecretory conditions is unknown.

2.4 Administration Instructions

Preparation of Constituted Suspension by a Healthcare Provider Prior to Dispensing

- Prior to dispensing, constitute famotidine for oral suspension by slowly adding 46 mL of Purified Water to the bottle. Shake vigorously for 5 to 10 seconds immediately after adding the water.
- The constituted suspension contains 40 mg of famotidine per 5 mL, and should be a smooth, mobile, white to off-white, and homogeneous suspension.

Administration and Storage of Constituted Suspension

- Shake the bottle of constituted famotidine for oral suspension vigorously for 5 to 10 seconds prior to each use.
- Take famotidine for oral suspension once daily before bedtime or twice daily in the morning and before bedtime, as recommended.
- Famotidine for oral suspension may be taken with or without food [see CLINICAL PHARMACOLOGY (12.3)].
- Famotidine for oral suspension may be given with antacids.
- Store the constituted suspension at 25°C (77°F). Protect from freezing. Discard unused constituted suspension after 30 days.

3 DOSAGE FORMS AND STRENGTHS

For Oral Suspension: 400 mg as a white to off-white powder. When constituted as directed, famotidine for oral suspension USP is a white to off-white powder forming a white to off-white suspension with characteristic odor, containing 40 mg of famotidine per 5 mL.

4 CONTRAINDICATIONS

Famotidine for oral suspension is contraindicated in patients with a history of serious hypersensitivity reactions (e.g., anaphylaxis) to famotidine or other histamine-2 (H2) receptor antagonists.

5 WARNINGS AND PRECAUTIONS

5.1 Central Nervous System Adverse Reactions

Central nervous system (CNS) adverse reactions, including confusion, delirium, hallucinations, disorientation, agitation, seizures, and lethargy, have been reported in elderly patients and patients with moderate and severe renal impairment treated with famotidine. Since famotidine blood levels are higher in patients with renal impairment than in patients with normal renal function, dosage adjustments are recommended in patients with renal impairment [see DOSAGE AND ADMINISTRATION (2.2), CLINICAL PHARMACOLOGY (12.3)].

5.2 Concurrent Gastric Malignancy

In adults, symptomatic response to therapy with famotidine for oral suspension does not preclude the presence of gastric malignancy. Consider evaluation for gastric malignancy in adult patients who have a suboptimal response or an early symptomatic relapse after completing treatment with famotidine for oral suspension.

6 ADVERSE REACTIONS

6.1 Clinical Trial Experience

Because clinical trials are conducted under widely varying conditions, adverse reaction rates observed in the clinical trials of a drug cannot be directly compared to rates in the clinical trials of another drug and may not reflect the rates observed in practice.

The safety of famotidine for oral suspension has been established based on adequate and well-controlled studies of another oral famotidine product [see CLINICAL STUDIES (14)]. The following is a summary of the adverse reactions reported in those studies.

Oral famotidine was studied in 7 US and international placebo- and active-controlled trials in approximately 2500 patients [see CLINICAL STUDIES (14)]. A total of 1442 patients were treated with famotidine, including 302 treated with 40 mg twice daily, 456 treated with 20 mg twice daily, 461 treated with 40 mg once daily, and 396 treated with 20 mg once daily. The population was 17 to 91 years old, fairly well distributed between sex and race; however, the predominant race was Caucasian.

The following adverse reactions occurred in greater than or equal to 1% of famotidine-treated patients: headache, dizziness and constipation.

The following other adverse reactions were reported in less than 1% of patients in clinical trials:

Body as a Whole: fever, asthenia, fatigue

Cardiovascular: palpitations

Gastrointestinal: elevated liver enzymes, vomiting, nausea, abdominal discomfort, anorexia, dry mouth

Hematologic: thrombocytopenia

Hypersensitivity: orbital edema, rash, conjunctival injection, bronchospasm

Musculoskeletal: musculoskeletal pain, arthralgia

Nervous System/Psychiatric: seizure, hallucinations, depression, anxiety, decreased libido, insomnia, somnolence

Skin: pruritus, dry skin, flushing

Special Senses: tinnitus, taste disorder

Other: impotence

Pediatric Patients Less Than One Year of Age

In a clinical study in 35 pediatric patients less than 1 year of age with GERD symptoms, two patients discontinued due to adverse reactions. Agitation observed in 5 patients resolved when famotidine was discontinued [see USE IN SPECIFIC POPULATIONS (8.4)].

6.2 Postmarketing Experience

The following adverse reactions have been identified during post-approval use of famotidine. Because these reactions are reported voluntarily from a population of uncertain size, it is not always possible to reliably estimate their frequency or establish a causal relationship to drug exposure.

Cardiovascular: arrhythmia, AV block, prolonged QT interval

Gastrointestinal: cholestatic jaundice, hepatitis

Hematologic: agranulocytosis, pancytopenia, leukopenia

Hypersensitivity: anaphylaxis, angioedema, facial edema, urticaria

Musculoskeletal: rhabdomyolysis, muscle cramps

Nervous System/Psychiatric: confusion, agitation, paresthesia

Respiratory: interstitial pneumonia

Skin: toxic epidermal necrolysis/Stevens-Johnson syndrome

7 DRUG INTERACTIONS

7.1 Drugs Dependent on Gastric pH for Absorption

Famotidine can reduce the absorption of other drugs, due to its effect on reducing intragastric acidity, leading to loss of efficacy of the concomitant drug.

Concomitant administration of famotidine for oral suspension with dasatinib, delavirdine mesylate, cefditoren, and fosamprenavir is not recommended.

See the prescribing information for other drugs dependent on gastric pH for absorption for administration instructions, including atazanavir, erlotinib, ketoconazole, itraconazole, ledipasvir/sofosbuvir, nilotinib, and rilpivirine.

7.2 Tizanidine (CYP1A2 Substrate)

Although not studied clinically, famotidine is considered a weak CYP1A2 inhibitor and may lead to substantial increases in blood concentrations of tizanidine, a CYP1A2 substrate. Avoid concomitant use with famotidine for oral suspension. If concomitant use is necessary, monitor for hypotension, bradycardia or excessive drowsiness. Refer to the full prescribing information for tizanidine.

8 USE IN SPECIFIC POPULATIONS

8.1 Pregnancy

Risk Summary

Available data with H2-receptor antagonists, including famotidine, in pregnant women are insufficient to establish a drug-associated risk of major birth defects, miscarriage or adverse maternal or fetal outcomes. In animal reproduction studies, no adverse development effects were observed with oral administration of famotidine at doses up to approximately 243 and 122 times, respectively, the recommended human dose of 80 mg per day for the treatment of erosive esophagitis (see Data).

The estimated background risk for major birth defects and miscarriage for the indicated population is unknown. All pregnancies have a background risk of birth defect, loss, or other adverse outcomes. In the U.S. general population, the background risk of major birth defects and miscarriage in clinically recognized pregnancies is 2 to 4% and 15 to 20%, respectively.

Data

Animal Data:

Reproductive studies have been performed in rats and rabbits at oral doses of up to 2000 and 500 mg/kg/day, respectively, and in both species at intravenous doses of up to 200 mg/kg/day, and have revealed no significant evidence of impaired fertility or harm to the fetus due to famotidine. While no direct fetotoxic effects have been observed, sporadic abortions occurring only in mothers displaying marked decreased food intake were seen in some rabbits at oral doses of 200 mg/kg/day (about 49 times the recommended human dose of 80 mg per day, based on body surface area) or higher. There are, however, no adequate or well-controlled studies in pregnant women. Because animal reproductive studies are not always predictive of human response, this drug should be used during pregnancy only if clearly needed.

8.2 Lactation

Risk Summary

There are limited data available on the presence of famotidine in human breast milk. There were no effects on the breastfed infant. There are no data on famotidine effects on milk production. Famotidine is present in the milk of lactating rats (see Data).

The developmental and health benefits of breastfeeding should be considered along with the mother’s clinical need for famotidine and any potential adverse effects on the breastfed child from famotidine for oral suspension or from the underlying maternal condition.

Data

Animal Data:

Transient growth depression was observed in young rats suckling from mothers treated with maternotoxic doses of famotidine at least 600 times the usual human dose.

8.4 Pediatric Use

Peptic Ulcer Disease and GERD With or Without Esophagitis and Ulcerations

Pediatric Patients One Year to Less than 17 Years of Age:

The safety and effectiveness of famotidine for oral suspension have been established in pediatric patients 1 year to less than 17 years of age for the treatment of peptic ulcer disease and GERD with or without esophagitis and ulcerations. Use of famotidine in this age group is supported by evidence from adequate and well-controlled studies of famotidine in adults with additional pharmacokinetic and pharmacodynamic data in pediatric patients 1 year to less than 17 years of age [see DOSAGE AND ADMINISTRATION (2.1), CLINICAL PHARMACOLOGY (12.2, 12.3)]. The safety and effectiveness of famotidine for oral suspension for the treatment of peptic ulcer disease in pediatric patients less than one year of age have not been established.

GERD

Pediatric Patients Less Than One Year of Age:

The safety and effectiveness of famotidine for oral suspension have been established in pediatric patients from birth to less than 1 year of age for the treatment of GERD. The use of famotidine this is age group is supported by evidence from adequate and well-controlled studies of famotidine in adults and with supportive data in pediatric patients from birth to less than 1 year of age [see DOSAGE AND ADMINISTRATION (2.1), CLINICAL PHARMACOLOGY (12.2, 12.3), CLINICAL STUDIES (14.7)].

Other Conditions

The safety and effectiveness for the treatment of pathological hypersecretory conditions and reduction of risk of duodenal ulcer recurrence have not been established in pediatric patients.

A safe and effective dosage has not been established in pediatric patients with renal impairment.

8.5 Geriatric Use

Of the 1442 famotidine-treated patients in clinical studies, approximately 10% were 65 and older. In these studies, no overall differences in safety or effectiveness were observed between elderly and younger patients. In postmarketing experience, CNS adverse reactions have been reported in elderly patients with and without renal impairment receiving famotidine [see WARNINGS AND PRECAUTIONS (5.1)].

Famotidine is known to be substantially excreted by the kidney, and the risk of adverse reactions to famotidine for oral suspension may be greater in elderly patients, particularly those with impaired renal function [see USE IN SPECIFIC POPULATIONS (8.6)].

In general, use the lowest effective dose of famotidine for oral suspension for an elderly patient and monitor renal function [see DOSAGE AND ADMINISTRATION (2.2)].

8.6 Renal Impairment

CNS adverse reactions and prolonged QT intervals have been reported in patients with moderate and severe renal impairment [see WARNINGS AND PRECAUTIONS (5.1)]. The clearance of famotidine is reduced in adults with moderate and severe renal impairment compared to adults with normal renal function [see CLINICAL PHARMACOLOGY (12.3)]. No dosage adjustment is needed in adults with mild renal impairment (creatinine clearance greater than or equal to 60 mL/minute). Dosage reduction is recommended in adults with moderate or severe renal impairment (creatinine clearance less than 60 mL/minute) [see DOSAGE AND ADMINISTRATION (2.3)]. Data are not available to establish a safe and effective dosage in pediatric patients with renal impairment.

10 OVERDOSAGE

The types of adverse reactions in overdosage of famotidine are similar to the adverse reactions encountered with use of recommended dosages [see ADVERSE REACTIONS (6.1)].

In the event of overdosage, treatment should be symptomatic and supportive. Unabsorbed material should be removed from the gastrointestinal tract, the patient should be monitored, and supportive therapy should be employed.

Due to low binding to plasma proteins, famotidine is eliminated by hemodialysis. There is limited experience on the usefulness of hemodialysis as a treatment for famotidine overdosage.

11 DESCRIPTION

The active ingredient in famotidine for oral suspension USP is a histamine-2 (H2) receptor antagonist. Famotidine is N'-(aminosulfonyl)-3-[[[2-[(diaminomethylene)amino]-4-thiazolyl]methyl]thio]propanimidamide. The empirical formula of famotidine is C8H15N7O2S3 and its molecular weight is 337.45. Its structural formula is:

Each 5 mL of famotidine for oral suspension USP when prepared as directed contains 40 mg of famotidine and the following inactive ingredients: anhydrous citric acid, powdered cellulose, sucrose, xanthan gum and banana, cherry and mint flavor. Added as preservatives are methylparaben sodium, propylparaben sodium and sodium benzoate.

Famotidine is a white to pale yellowish-white crystalline powder that is freely soluble in dimethyl formamide and glacial acetic acid; slightly soluble in methanol; very slightly soluble in water; and practically insoluble in chloroform, ether and ethyl acetate.

12 CLINICAL PHARMACOLOGY

12.1 Mechanism of Action

Famotidine is a competitive inhibitor of histamine-2 (H2) receptors. The primary clinically important pharmacologic activity of famotidine is inhibition of gastric secretion. Both the acid concentration and volume of gastric secretion are suppressed by famotidine, while changes in pepsin secretion are proportional to volume output.

12.2 Pharmacodynamics

Adults

Famotidine inhibited both basal and nocturnal gastric secretion, as well as secretion stimulated by food and pentagastrin. After oral administration of famotidine, the onset of the antisecretory effect occurred within one hour; the maximum effect was dose-dependent, occurring within one to three hours. Duration of inhibition of secretion by doses of 20 mg and 40 mg was 10 to 12 hours.

Single evening oral doses of 20 mg and 40 mg inhibited basal and nocturnal acid secretion in all subjects; mean nocturnal gastric acid secretion was inhibited by 86% and 94%, respectively, for a period of at least 10 hours. The same doses given in the morning suppressed food-stimulated acid secretion in all subjects. The mean suppression was 76% and 84%, respectively, 3 to 5 hours after administration, and 25% and 30%, respectively, 8 to 10 hours after administration. In some subjects who received the 20 mg dose, however, the antisecretory effect was dissipated within 6 to 8 hours. There was no cumulative effect with repeated doses. The nocturnal intragastric pH was raised by evening doses of 20 mg and 40 mg of famotidine to mean values of 5.0 and 6.4, respectively. When famotidine was given after breakfast, the basal daytime interdigestive pH at 3 and 8 hours after 20 mg or 40 mg of famotidine was raised to about 5.

Famotidine had little or no effect on fasting or postprandial serum gastrin levels. Gastric emptying and exocrine pancreatic function were not affected by famotidine.

In clinical pharmacology studies, systemic effects of famotidine in the CNS, cardiovascular, respiratory or endocrine systems were not noted. Also, no anti-androgenic effects were noted. Serum hormone levels, including prolactin, cortisol, thyroxine (T4), and testosterone, were not altered after treatment with famotidine.

Pediatric Patients

Pharmacodynamics of famotidine, assessed by gastric pH, were evaluated in 5 pediatric patients 2 years to 13 years of age using the sigmoid Emax model. These data suggest that the relationship between serum concentration of famotidine and gastric acid suppression is similar to that observed in adults (see Table 4).

Table 4: Serum Concentrations of Famotidine Associated with Gastric Acid Reduction in Famotidine- Treated Pediatric and Adult Patientsa
 | EC50(ng/mL)a
Pediatric Patients | 26 ± 13
Adults
Healthy adult subjects | 26.5 ± 10.3
Adult patients with upper GI bleeding | 18.7 ± 10.8

a Using the Sigmoid Emax model, serum concentrations of famotidine associated with 50% maximum gastric acid reduction are presented as means ± SD.

In a study examining the effect of famotidine on gastric pH and duration of acid suppression in pediatric patients, four pediatric patients ages 11 to 15 years of age using the oral formulation at a dose of 0.5 mg/kg, maintained a gastric pH above 5 for 13.5 ± 1.8 hours.

12.3 Pharmacokinetics

Absorption

Famotidine is incompletely absorbed. The bioavailability of oral doses is 40 to 45%. Bioavailability may be slightly increased by food, or slightly decreased by antacids; however, these effects are of no clinical consequence.

Peak famotidine plasma levels occur in 1 to 3 hours. Plasma levels after multiple dosages are similar to those after single doses.

Distribution

Fifteen to 20% of famotidine in plasma is protein bound.

Elimination

Metabolism:

Famotidine undergoes minimal first-pass metabolism. Twenty-five to 30% of an oral dose was recovered in the urine as unchanged compound. The only metabolite identified in humans is the S-oxide.

Excretion:

Famotidine has an elimination half-life of 2.5 to 3.5 hours. Famotidine is eliminated by renal (65 to 70%) and metabolic (30 to 35%) routes. Renal clearance is 250 to 450 mL/minute, indicating some tubular excretion.

Specific Populations

Pediatric Patients:

Infants from birth to 12 Months

After a single oral dose administration of 0.5 mg/kg orally in patients from birth to 12 months, the bioavailability is approximately 42%.

The AUC increased 1.4-fold after single oral dose of 1 mg/kg compared to 0.5 mg/kg and 2.7-fold after multiple oral doses of 1 mg/kg compared to 0.5 mg/kg.

Plasma clearance is reduced and elimination half-life is prolonged in pediatric patients from birth to 3 months of age compared to older pediatric patients. Following intravenous administration of 0.5 mg/kg, CLTotal was 0.13 ± 0.06 L/hr/kg, 0.21 ± 0.06 L/hr/kg, and 0.49 ± 0.17 L/hr/kg in pediatric patients <1 month of age, <3 months of age, and >3 to 12 months of age, respectively. Elimination half-life was 10.5 hours, 8.1 hours, and 4.5 hours in pediatric patients <1 month of age, <3 months of age, and >3 to 12 months of age, respectively.

Patients 11 Years to 15 Years

The mean bioavailability in 8 pediatric patients was 50% compared to adult values of 42% to 49%.

Pharmacokinetic parameters in pediatrics 11 years to 15 years is compared to infants from birth to 12 months in Table 5.

Table 5: Mean Pharmacokinetic Parameters Following a Single Oral Dose of 0.5 mg/kg in Infants and Pediatric Patients
 | Infants from Birth to 12 Months (N=5) | Pediatric Patients 11 Years to 15 Years (N=8)
AUC0 to ∞ (ng*hr/mL)a | 645 ± 249 | 580 ± 60
Cmax (ng/mL) | 79.2 | 97.3
Tmax (hr)b | 2.0 (1.0, 4.1)c | 2.3 (2.1, 2.9)d
T1/2(hr) | 5.82 | 2.13

a arithmetic mean ± S.D.
b median
c observed minimum and maximum values
d reported minimum and maximum values

Patients with Renal Impairment:

In adult patients with severe renal impairment (creatinine clearance less than 30 mL/minute), the systemic exposure (AUC) of famotidine increased at least 5-fold. In adult patients with moderate renal impairment (creatinine clearance between 30 to 60 mL/minute), the AUC of famotidine increased at least 2-fold [see DOSAGE AND ADMINISTRATION (2.3), USE IN SPECIFIC POPULATIONS (8.6)].

Drug Interaction Studies

Human Organic Anion Transporter (OAT) 1 and 3:

In vitro studies indicate that famotidine is a substrate for OAT1 and OAT3. Following coadministration of probenecid (1500 mg), an inhibitor of OAT1 and OAT3, with a single oral 20 mg dose of famotidine in 8 healthy subjects, the serum AUC0 to 10h of famotidine increased from 424 to 768 ng•hr/mL and the maximum serum concentration (Cmax) increased from 73 to 113 ng/mL. Renal clearance, urinary excretion rate and amount of famotidine excreted unchanged in urine were decreased. The clinical relevance of this interaction is unknown.

Multidrug and Toxin Extrusion Protein 1 (MATE-1):

An in vitro study showed that famotidine is an inhibitor of MATE-1. However, no clinically significant interaction with metformin, a substrate for MATE-1, was observed.

CYP1A2:

Famotidine is a weak CYP1A2 inhibitor.

13 NONCLINICAL TOXICOLOGY

13.1 Carcinogenesis, Mutagenesis, Impairment of Fertility

Carcinogenic potential of famotidine was assessed in a 106-week oral carcinogenicity study in rats and a 92-week oral carcinogenicity study in mice. In the 106-week study in rats and the 92-week study in mice at oral doses of up to 2000 mg/kg/day (approximately 243 and 122 times, respectively, based on body surface area, the recommended human dose of 80 mg per day for the treatment of erosive esophagitis), there was no evidence of carcinogenic potential for famotidine.

Famotidine was negative in the microbial mutagen test (Ames test) using Salmonella typhimurium and Escherichia coli with or without rat liver enzyme activation at concentrations up to 10,000 mcg/plate. In in vivo studies in mice, with a micronucleus test and a chromosomal aberration test, no evidence of a mutagenic effect was observed.

In studies with rats given oral doses of up to 2000 mg/kg/day (approximately 243 times, based on body surface area, the recommended human dose of 80 mg per day) fertility and reproductive performance were not affected.

14 CLINICAL STUDIES

The safety and effectiveness of famotidine for oral suspension have been established based on adequate and well-controlled studies of another oral famotidine product. The following is a summary of the efficacy results reported in those studies.

14.1 Active Duodenal Ulcer

In a U.S. multicenter, double-blind trial in adult outpatients with endoscopically confirmed duodenal ulcer (DU), orally administered famotidine was compared to placebo. As shown in Table 6, 70% of patients treated with famotidine 40 mg at bedtime were healed by Week 4. Most patients' DU healed within 4 weeks.

Patients not healed by Week 4 were continued in the trial. By Week 8, 83% of patients treated with famotidine had healed DU, compared to 45% of patients treated with placebo. The incidence of DU healing with famotidine was greater than with placebo at each time point based on proportion of endoscopically confirmed healed DUs. Trials have not assessed the safety of famotidine in uncomplicated active DU for periods of more than 8 weeks.

Table 6: Patients with Endoscopically Confirmed Healed Duodenal Ulcers
 | Famotidine; 40 mg at bedtime (N=89) | Famotidine; 20 mg twice daily (N=84) | Placebo; at bedtime; (N=97)
Week 2 | 32%a | 38% a | 17%
Week 4 | 70% a | 67% a | 31%

ap<0.001 vs. placebo

In this study, time to relief of daytime and nocturnal pain was shorter for patients receiving famotidine than for patients receiving placebo; patients receiving famotidine also took less antacid than patients receiving placebo.

14.2 Active Gastric Ulcer

In both a U.S. and an international multicenter, double-blind trials in patients with endoscopically confirmed active gastric ulcer (GU), orally administered famotidine 40 mg at bedtime was compared to placebo. Antacids were permitted during the trials, but consumption was not significantly different between the famotidine and placebo groups.

As shown in Table 7, the incidence of GU healing confirmed by endoscopy (dropouts counted as unhealed) with famotidine was greater than placebo at Weeks 6 and 8 in the U.S. trial, and at Weeks 4, 6 and 8 in the international trial.

In these trials, most famotidine-treated patients healed within 6 weeks. Trials have not assessed the safety of famotidine in uncomplicated active GU for periods of more than 8 weeks.

Table 7: Patients with Endoscopically Confirmed Healed Gastric Ulcers
 | U.S. Study (N=149) |  | International Study (N=294)
 | Famotidine; 40 mg at bedtime (N=74) | Placebo; at bedtime (N=75) | Famotidine; 40 mg at bedtime (N=149) | Placebo; at bedtime (N=145)
Week 4 | 45% | 39% | 47% a | 31%
Week 6 | 66%a | 44% | 65% a | 46%
Week 8 | 78%b | 64% | 80% a | 54%

a p≤0.01 vs. placebo
b p≤0.05 vs. placebo

Time to complete relief of daytime and nighttime pain was statistically significantly shorter for patients receiving famotidine than for patients receiving placebo; however, neither trial demonstrated a statistically significant difference in the proportion of patients whose pain was relieved by the end of the trial (Week 8).

14.3 Symptomatic Gastroesophageal Reflux Disease (GERD)

Orally administered famotidine was compared to placebo in a U.S. trial that enrolled patients with symptoms of GERD and without endoscopic evidence of esophageal erosion or ulceration. As shown in Table 8, patients treated with famotidine 20 mg twice daily had greater improvement in symptomatic GERD than patients treated with 40 mg at bedtime or placebo.

Table 8: Patients with Improvement of Symptomatic GERD (N=376)
 | Famotidine; 20 mg twice daily (N=154) | Famotidine; 40 mg at bedtime (N=149) | Placebo; at bedtime (N=73)
Week 6 | 82%a | 69% | 62%

a p≤0.01 vs. placebo

14.4 Erosive Esophagitis due to GERD

Healing of endoscopically verified erosion and symptomatic improvement were studied in a U.S. and an international double-blind trials. Healing was defined as complete resolution of all erosions visible with endoscopy. The U.S. trial comparing orally administered famotidine 40 mg twice daily to placebo and orally administered famotidine 20 mg twice daily showed a significantly greater percentage of healing of erosive esophagitis for famotidine 40 mg twice daily at Weeks 6 and 12 (Table 9).

Table 9: Patients with Endoscopic Healing of Erosive Esophagitis - U.S. Study (N=318)
 | Famotidine; 40 mg twice daily (N=127) | Famotidine; 20 mg twice daily (N=125) | Placebo; twice daily (N=66)
Week 6 | 48%a,b | 32% | 18%
Week 12 | 69%a,c | 54%a | 29%

a p≤0.01 vs. placebo
b p≤0.01 vs. famotidine 20 mg twice daily
c p≤0.05 vs. famotidine 20 mg twice daily

As compared to placebo, patients in the U.S. trial who received famotidine had faster relief of daytime and nighttime heartburn, and a greater percentage of famotidine-treated patients experienced complete relief of nighttime heartburn. These differences were statistically significant.

In the international trial, when orally administered famotidine 40 mg twice daily was compared to orally administered ranitidine 150 mg twice daily, a statistically significantly greater percentage of healing of erosive esophagitis was observed with famotidine 40 mg twice daily at Week 12 (Table 10). There was, however, no significant difference in symptom relief among treatment groups.

Table 10: Patients with Endoscopic Healing of Erosive Esophagitis - International Study (N=440)
 | Famotidine; 40 mg twice daily (N=175) | Famotidine; 20 mg twice daily (N=93) | Ranitidine; 150 mg twice daily (N=172)
Week 6 | 48% | 52% | 42%
Week 12 | 71%a | 68% | 60%

a p≤0.05 vs ranitidine 150 mg twice daily

14.5 Pathological Hypersecretory Conditions

In trials of patients with pathological hypersecretory conditions such as Zollinger-Ellison syndrome with or without multiple endocrine neoplasias, famotidine significantly inhibited gastric acid secretion and controlled associated symptoms. Orally administered famotidine dosages from 20 mg to 160 mg every 6 hours maintained basal acid secretion below 10 mEq/hour; initial dosages were titrated to the individual patient need and subsequent adjustments were necessary with time in some patients.

14.6 Risk Reduction of Duodenal Ulcer Recurrence

Two randomized, double-blind, multicenter trials in patients with endoscopically confirmed healed DUs demonstrated that patients receiving treatment with orally administered famotidine 20 mg at bedtime had lower rates of DU recurrence, as compared with placebo.

- In the U.S. trial, DU recurrence within 12 months was 2.4 times greater in patients treated with placebo than in the patients treated with famotidine. The 89 famotidine-treated patients had a cumulative observed DU recurrence rate of 23%, compared to a 57% in the 89 patients receiving placebo (p<0.01).
- In the international trial, the cumulative observed DU recurrence within 12 months in the 307 famotidine-treated patients was 36%, compared to 76% in the 325 patients who received placebo (p<0.01).

Controlled trials have not extended beyond one year.

14.7 GERD in Pediatric Patients Less Than 1 Year of Age

In a double-blind, randomized, treatment-withdrawal study, 35 pediatric patients less than 1 year of age who were diagnosed with GERD, primarily by history of vomiting (spitting up) and irritability (fussiness), were treated for up to 4 weeks with famotidine oral suspension 0.5 mg/kg or 1 mg/kg administered once daily for patients less than 3 months of age and administered twice daily for patients 3 months to less than 12 months of age. Caregivers were instructed to provide conservative treatment including thickened feedings. After 4 weeks of treatment, patients were randomly withdrawn from the treatment and followed an additional 4 weeks for vomiting (spitting up), irritability (fussiness) and global assessments of improvement. The study patients ranged in age at entry from 1.3 to 10.5 months (mean 5.6 ± 2.9 months), 57% were female, 91% were white and 6% were black. Most patients (27/35) continued into the treatment-withdrawal phase of the study. Most patients improved during the initial treatment phase of the study. Results of the treatment-withdrawal phase were difficult to interpret because of small numbers of patients.

16 HOW SUPPLIED/STORAGE AND HANDLING

Famotidine for Oral Suspension USP is a white to off-white powder forming a white to off-white suspension with characteristic odor on constitution, containing 40 mg of famotidine per 5 mL.

The suspension is a cherry-banana-mint flavored.

50 mL NDC: 72162-2599-2: Bottle containing 400 mg famotidine.

Prior to dispensing, constitute famotidine for oral suspension [see DOSAGE AND ADMINISTRATION (2.3)]

Storage

Store famotidine for oral suspension dry powder and constituted suspension at 25°C (77°F); excursions permitted to 15° to 30°C (59° to 86°F) [see USP Controlled Room Temperature].

Protect from freezing. Discard unused constituted suspension after 30 days.

Dispense in a USP tight, light-resistant container.

Repackaged/Relabeled by:
Bryant Ranch Prepack, Inc.
Burbank, CA 91504

17 PATIENT COUNSELING INFORMATION

Central Nervous System (CNS) Adverse Reactions

Advise elderly patients and those with moderate and severe renal impairment of the risk of CNS adverse reactions, including confusion, delirium, hallucinations, disorientation, agitation, seizures, and lethargy [see WARNINGS AND PRECAUTIONS (5.1)]. Report symptoms immediately to a healthcare provider.

QT Prolongation

Advise patients with moderate and severe renal impairment of the risk of QT interval prolongation [see USE IN SPECIFIC POPULATIONS (8.6)]. Report new cardiac symptoms, such as palpitations, fainting and dizziness or lightheadedness immediately to a healthcare provider.

Administration

Advise patients to take and caregivers to administer:

- Famotidine for oral suspension once daily before bedtime or twice daily in the morning and before bedtime, as recommended.

Advise patients and caregivers:

- Famotidine for oral suspension may be taken with or without food.
- Famotidine for oral suspension may be given with antacids.

Manufactured by:

Carnegie Pharmaceuticals LLC
Delran, NJ 08075, USA

Revised: July, 2022

PACKAGE LABEL

Famotidine 40mg/5mL Powder for Susp #50